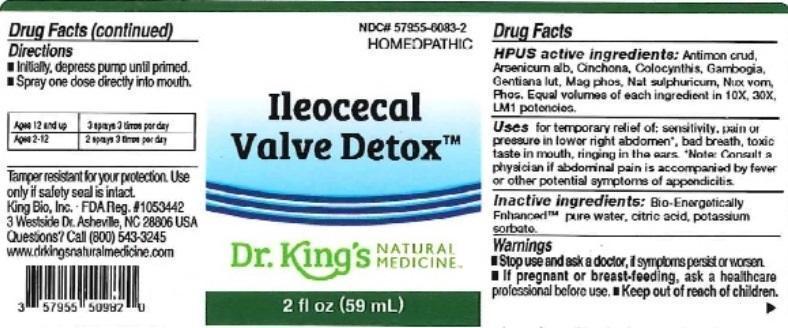 DRUG LABEL: Ileocecal Valve Detox
NDC: 57955-6083 | Form: LIQUID
Manufacturer: King Bio Inc.
Category: homeopathic | Type: HUMAN OTC DRUG LABEL
Date: 20160413

ACTIVE INGREDIENTS: ANTIMONY TRISULFIDE 10 [hp_X]/59 mL; ARSENIC TRIOXIDE 10 [hp_X]/59 mL; CINCHONA OFFICINALIS BARK 10 [hp_X]/59 mL; CITRULLUS COLOCYNTHIS FRUIT PULP 10 [hp_X]/59 mL; GAMBOGE 10 [hp_X]/59 mL; GENTIANA LUTEA ROOT 10 [hp_X]/59 mL; MAGNESIUM PHOSPHATE, DIBASIC TRIHYDRATE 10 [hp_X]/59 mL; SODIUM SULFATE 10 [hp_X]/59 mL; STRYCHNOS NUX-VOMICA SEED 10 [hp_X]/59 mL; PHOSPHORUS 10 [hp_X]/59 mL
INACTIVE INGREDIENTS: WATER; ANHYDROUS CITRIC ACID; POTASSIUM SORBATE

Ileocecal Valve Detox™

ACTIVE INGREDIENT

Drug Facts__________________________________________________________________________________________________________

HPUS active ingredients: Antimonium crudum, Arsenicum album, Cinchona officinalis, Colocynthis, Gambogia, Gentiana lutea, Magnesia phosphorica, Natrum sulphuricum, Nux vomica, Phosphorus. Equal volumes of each ingredient in 10X, 30X, LM1 potencies.

INDICATIONS AND USAGE

Uses for temporary relief of: sensitivity, pain or pressure in lower right abdomen, bad breath, toxic taste in mouth, ringing in the ears.

Note: Consult a physician if abdominal pain is accompanied by fever or other potential symptoms of appendicitis.

Inactive Ingredients:

Bio-Energetically Enhanced™ pure water, citric acid and potassium sorbate.

Warnings

- Stop use and ask your doctor if symptoms persist or worsen.
- If pregnant or breast-feeding, ask a healthcare professional before use.

- Keep out of reach of children.

Directions

- Initially, depress pump until primed.
- Spray one dose directly into mouth.
- Ages 12 and up: 3 sprays 3 times per day.
- Ages 2-12: 2 sprays 3 times per day.

OTHER SAFETY INFORMATION

Tamper resistant for your protection. Use only if seal is intact.

PURPOSE

Uses for temporary relief of: •sensitivity, pain or pressure in lower right abdomen •bad breath •toxic taste in mouth •ringing in the ears.

Note: Consult a physician if abdominal pain is accompanied by fever or other potential symptoms of appendicitis.